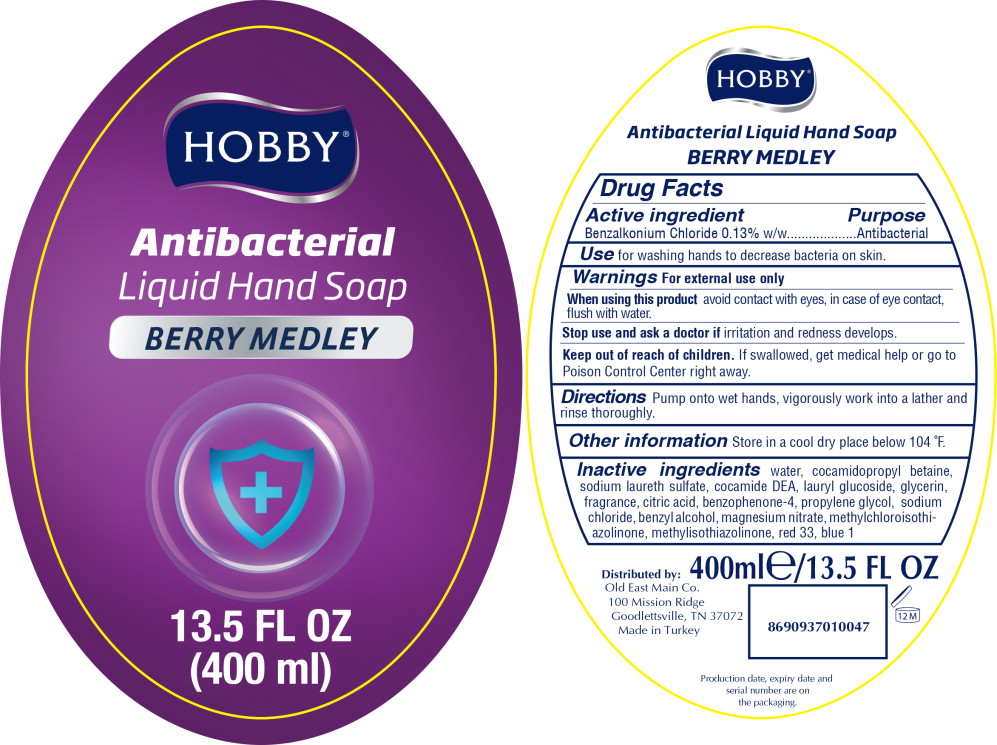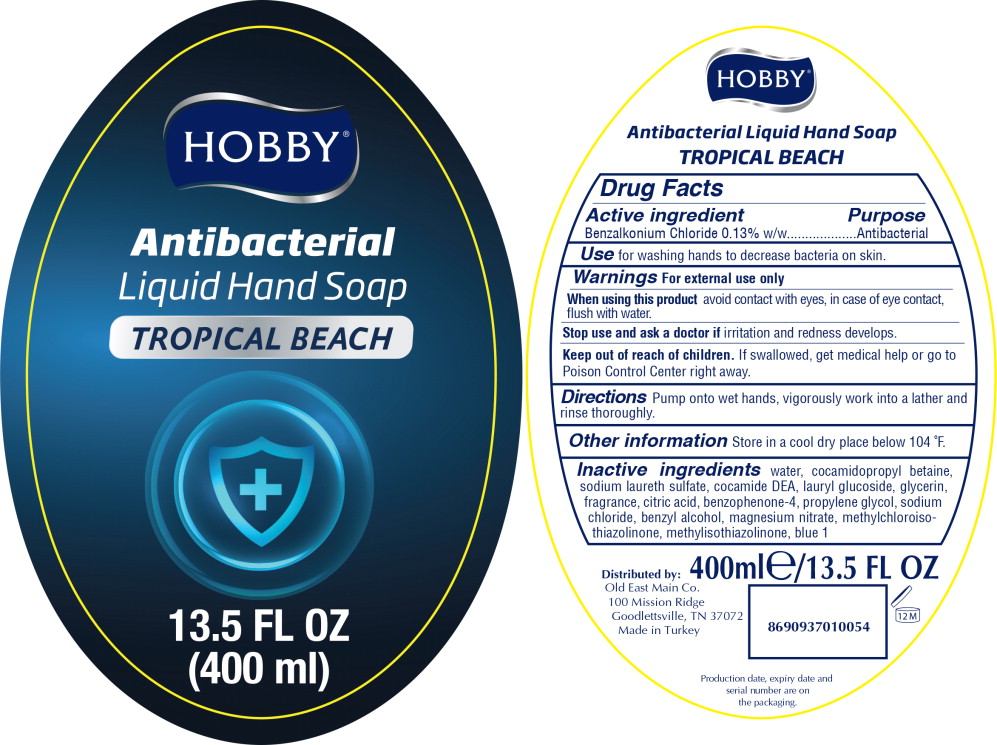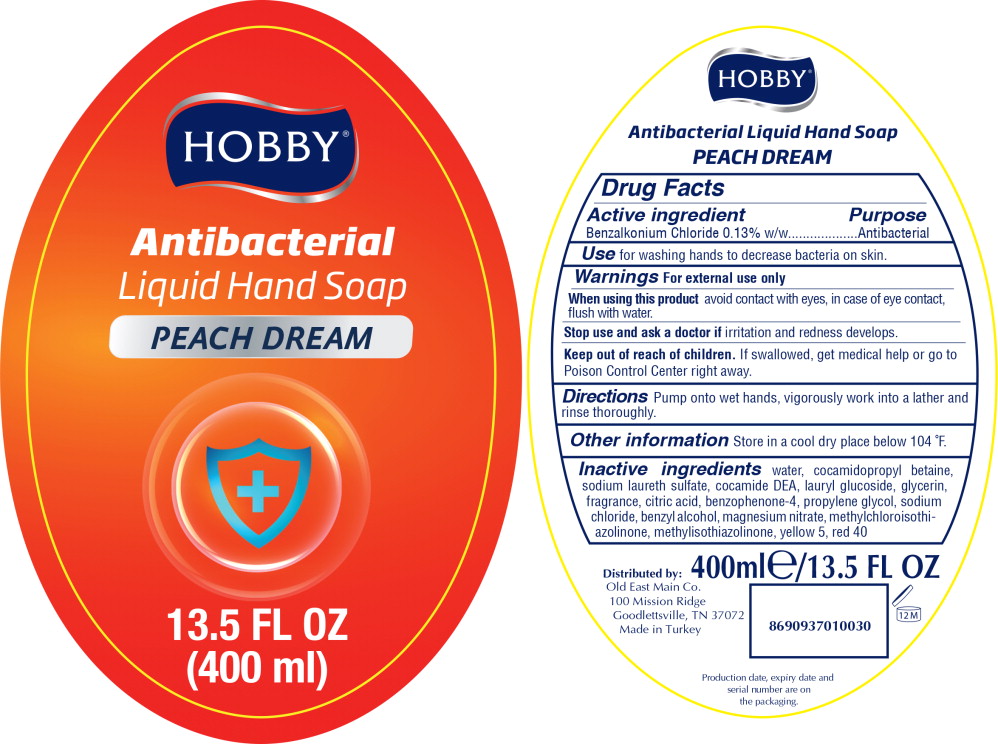 DRUG LABEL: HOBBY ANTIBACTERIAL HANDWASH
NDC: 73789-0442 | Form: LIQUID
Manufacturer: Hobi Kozmetik Imalat Sanayi Ve Ticaret Anonim Sirketi
Category: otc | Type: HUMAN OTC DRUG LABEL
Date: 20201023

ACTIVE INGREDIENTS: BENZALKONIUM CHLORIDE 0.13 g/100 mL
INACTIVE INGREDIENTS: METHYLCHLOROISOTHIAZOLINONE; METHYLISOTHIAZOLINONE; CITRIC ACID MONOHYDRATE; SODIUM CHLORIDE; WATER; SODIUM LAURETH SULFATE; COCAMIDOPROPYL BETAINE; COCO DIETHANOLAMIDE; FD&C RED NO. 40; FD&C BLUE NO. 1; LIMONENE, (+)-; D&C RED NO. 33; GLYCERIN; SULISOBENZONE; LAURYL GLUCOSIDE; FD&C YELLOW NO. 5; BENZYL ALCOHOL; EDETATE DISODIUM ANHYDROUS; Magnesium Citrate; Propylene Glycol; LINALOOL, (+/-)-; FD&C YELLOW NO. 6; Benzyl Benzoate; Benzyl Salicylate; .ALPHA.-HEXYLCINNAMALDEHYDE; Magnesium Nitrate

Drug Facts

Active ingredient

Benzalkonium Chloride 0.13% w/w

Purpose

Antibacterial

Use

for washing hands to decrease bacteria on skin.

Warnings

For external use only

When using this product avoid contact with eyes, in case of eye contact, flush with water.

Stop use and ask a doctor if irritation and redness develops.

Keep out of reach of children. If swallowed, get medical help or go to Poison Control Center right away.

Directions

Pump onto wet hands, vigorously work into a lather and rinse thoroughly.

Other information

Store in a cool dry place below 104 °F.

Inactive ingredients

water, cocamidopropyl betaine, sodium laureth sulfate, cocamide DEA, lauryl glucoside, glycerin, fragrance, citric acid, benzophenone-4, propylene glycol, sodium chloride, benzyl alcohol, magnesium nitrate, methyIchloroisothiazolinone, methylisothiazolinone, red 33, blue 1

Principal Display Panel - 400 mL Label

HOBBY®

Antibacterial
Liquid Hand Soap

BERRY MEDLEY

13.5 FL OZ
(400 ml)

Principal Display Panel - 400 mL Label

HOBBY®

Antibacterial
Liquid Hand Soap

TROPICAL BEACH

13.5 FL OZ
(400 ml)

Principal Display Panel - 400 mL Label

HOBBY®

Antibacterial
Liquid Hand Soap

PEACH DREAM

13.5 FL OZ
(400 ml)